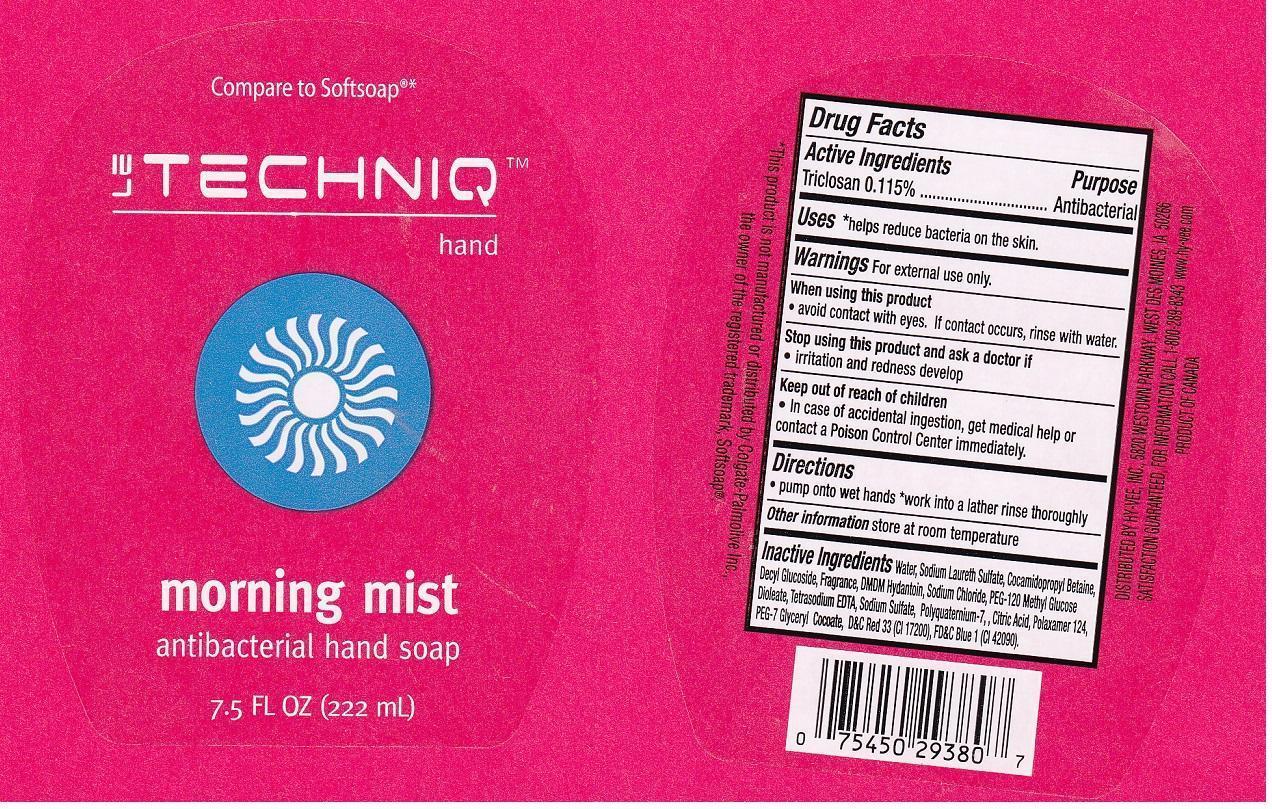 DRUG LABEL: LE TECHNIQ
NDC: 42507-719 | Form: LIQUID
Manufacturer: HYVEE INC
Category: otc | Type: HUMAN OTC DRUG LABEL
Date: 20140226

ACTIVE INGREDIENTS: TRICLOSAN 1.15 mg/1 mL
INACTIVE INGREDIENTS: WATER; SODIUM LAURETH SULFATE; COCAMIDOPROPYL BETAINE; DECYL GLUCOSIDE; DMDM HYDANTOIN; SODIUM CHLORIDE; PEG-120 METHYL GLUCOSE DIOLEATE; EDETATE SODIUM; SODIUM SULFATE; POLYQUATERNIUM-7 (70/30 ACRYLAMIDE/DADMAC; 1600000 MW); CITRIC ACID MONOHYDRATE; POLOXAMER 124; PEG-7 GLYCERYL COCOATE; D&C RED NO. 33; FD&C BLUE NO. 1

DRUG FACTS

ACTIVE INGREDIENT

TRICLOSAN 0.115%

PURPOSE

ANTIBACTERIAL

USES

HELPS REDUCE BACTERIA ON THE SKIN

WARNINGS

FOR EXTERNAL USE ONLY

WHEN USING THIS PRODUCT

AVOID CONTACT WITH EYES. IF CONTACT OCCURS, RINSE WITH WATER

STOP USING THIS PRODUCT AND ASK A DOCTOR IF

IRRITATION OR REDNESS DEVELOP

KEEP OUT OF REACH OF CHILDREN

IN CASE OF ACCIDENTAL INGESTION, GET MEDICAL HELP OR CONTACT A POISON CONTROL CENTER IMMEDIATELY

DIRECTIONS

PUMP ONTO WET HANDS. WORK INTO A LATHER RINSE THOROUGHLY

OTHER INFORMATION

STORE AT ROOM TEMPERATURE

INACTIVE INGREDIENTS

WATER, SODIUM LAURETH SULFATE, COCAMIDOPROPYL BETAINE, DECYL GLUCOSIDE, FRAGRANCE, DMDM HYDANTOIN, SODIUM CHLORIDE, PEG-120 METHYL GLUCOSE DIOLEATE, TETRASODIUM EDTA, SODIUM SULFATE, POLYQUATERNIUM-7, CITRIC ACID, POLOXAMER 124, PEG-7 GLYCERYL COCOATE, D&C RED 33 (CI 17200), FD&C BLUE 1 (CI 42090)